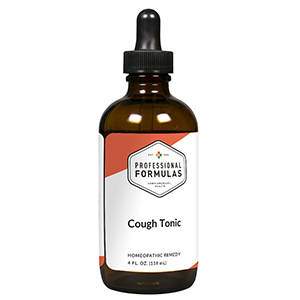 DRUG LABEL: Cough Tonic
NDC: 63083-2995 | Form: LIQUID
Manufacturer: Professional Complementary Health Formulas
Category: homeopathic | Type: HUMAN OTC DRUG LABEL
Date: 20190815

ACTIVE INGREDIENTS: SPONGIA OFFICINALIS SKELETON, ROASTED 2 [hp_X]/118 mL; ACONITUM NAPELLUS WHOLE 3 [hp_X]/118 mL; AMARYLLIS BELLADONNA WHOLE 3 [hp_X]/118 mL; BRYONIA ALBA ROOT 3 [hp_X]/118 mL; PULSATILLA MONTANA WHOLE 4 [hp_X]/118 mL; IPECAC 5 [hp_X]/118 mL; ARSENIC TRIOXIDE 6 [hp_X]/118 mL; DROSERA ROTUNDIFOLIA WHOLE 6 [hp_X]/118 mL
INACTIVE INGREDIENTS: ALCOHOL; WATER

CCT

ACTIVE INGREDIENTS

Spongia tosta 2X
Aconitum napellus 3X
Belladonna 3X
Bryonia 3X
Pulsatilla 4X
Ipecacuanha 5X
Arsenicum album 6X
Drosera rotundifolia 6X

QUESTIONS

Professional Formulas

PO Box 2034 Lake Oswego, OR 97035

INDICATIONS

Temporarily reduces the intensity of coughing and congestion.*

PURPOSE

*Claims based on traditional homeopathic practice, not accepted medical evidence. Not FDA evaluated.

WARNINGS

A persistent cough may be a sign of a serious condition. If cough persists, tends to recur, or is accompanied by a fever, rash, or other symptoms, consult a doctor. Keep out of the reach of children. In case of overdose, get medical help or contact a poison control center right away. If pregnant or breastfeeding, ask a healthcare professional before use.

Keep out of the reach of children.

PREGNANCY OR BREAST FEEDING

If pregnant or breastfeeding, ask a healthcare professional before use.

DIRECTIONS

Place liquid under tongue 30 minutes before/after meals. Adults and children 12 years and over: Take one teaspoon up to 2 times per day. Consult a physician for use in children under 12 years of age.

OTHER INFORMATION

Tamper resistant. If seal is broken, do not use. After opening, close container tightly and store at room temperature away from heat.

INACTIVE INGREDIENTS

Glycyrrhiza glabra root extract (1:1), polygala tenuifolia root extract (1:1), grindelia camporum aerial parts extract (1:1), inula helenium root extract (1:1), thymus vulgaris leaves extract (1:1), verbascum thapsus leaves extract (1:2), asclepias tuberosa root extract (1:1), zingiber officinale root extract (1:1), pimpinella anisum seed extract (1:1), 15% vegetable glycerin (from soy), 10% ethanol, 5% cherry extract, purified water.

LABEL

Est 1985

Professional Formulas

Complementary Health

Cough Tonic

Homeopathic Remedy

4 FL. OZ. (118 mL)